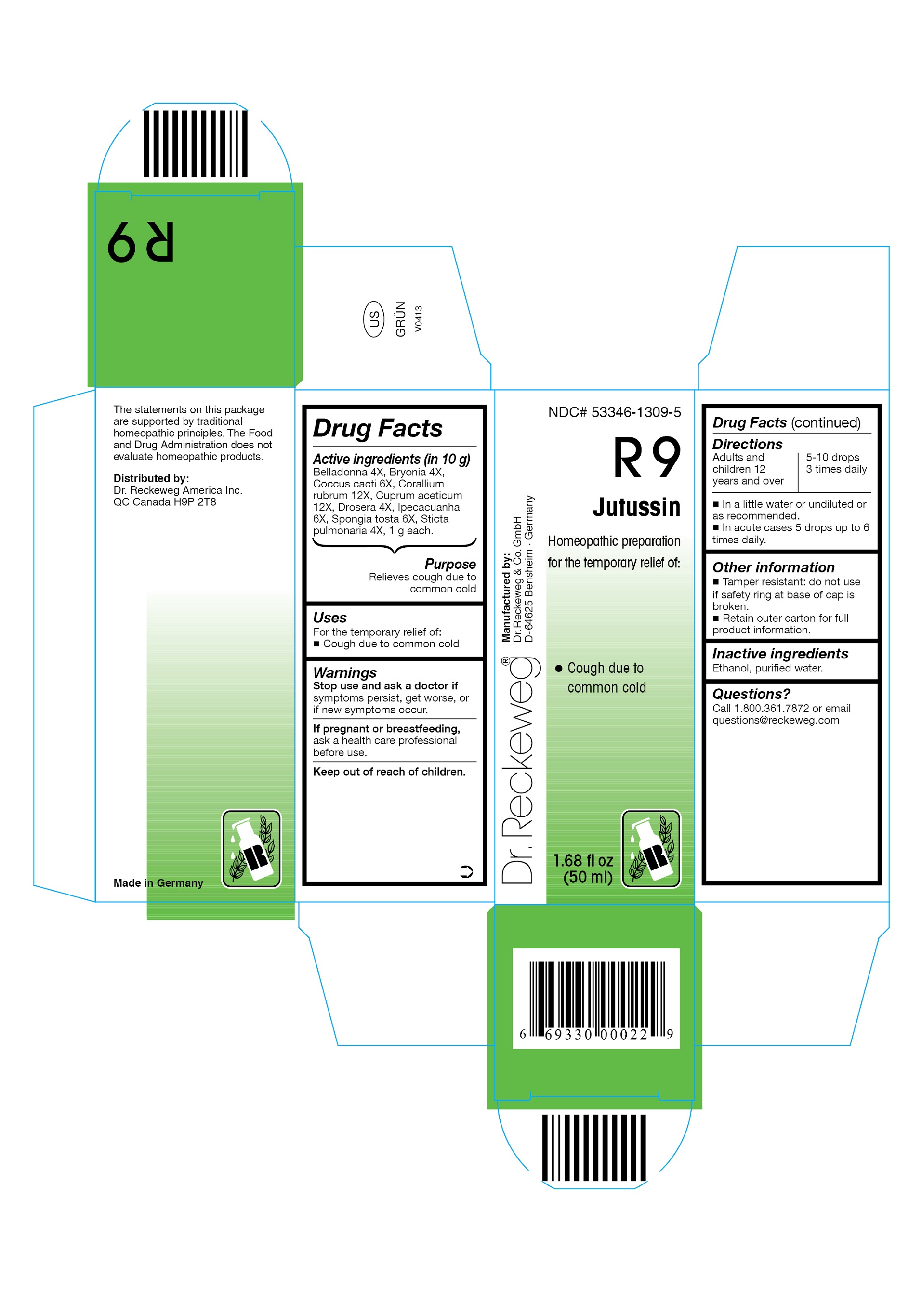 DRUG LABEL: DR. RECKEWEG R9 Jutussin
NDC: 53346-1309 | Form: LIQUID
Manufacturer: PHARMAZEUTISCHE FABRIK DR. RECKEWEG & CO
Category: homeopathic | Type: HUMAN OTC DRUG LABEL
Date: 20130403

ACTIVE INGREDIENTS: ATROPA BELLADONNA 4 [hp_X]/50 mL; BRYONIA DIOICA ROOT 4 [hp_X]/50 mL; PROTORTONIA CACTI 6 [hp_X]/50 mL; CORALLIUM RUBRUM EXOSKELETON 12 [hp_X]/50 mL; CUPRIC ACETATE 12 [hp_X]/50 mL; DROSERA ROTUNDIFOLIA 4 [hp_X]/50 mL; IPECAC 6 [hp_X]/50 mL; SPONGIA OFFICINALIS SKELETON, ROASTED 6 [hp_X]/50 mL; LOBARIA PULMONARIA 4 [hp_X]/50 mL
INACTIVE INGREDIENTS: ALCOHOL; WATER

DR. RECKEWEG R9 Jutussin

Active ingredients:

Belladonna 4X, Bryonia 4X, Coccus cacti 6X, Corallium rubrum 12X, Cuprum aceticum 12X, Drosera 4X, Ipecacuanha 6X, Spongia tosta 6X, Sticta pulmonaria 4X, 1 g each in 10 g.

Purpose

Relieves cough due to common cold

Uses

For the temporary relief of:

- Cough due to common cold

Warnings

Stop use and ask a doctor if symptoms persist, get worse, or if new symptoms occur.

PREGNANCY OR BREAST FEEDING

If pregnant or breastfeeding, ask a health care professional before use.

Keep out of reach of children.

Directions
Adults and children ≥ 12 years 5-10 drops 3 times daily; acute cases: 5 drops

up to 6 times daily in a little water or undiluted or as recommended.

Other information

- Tamper resistant: do not use if safety ring at base of cap is broken.
- Retain outer carton for full product information.

Inactive ingredients

Ethanol, purified water.

Questions?

Call 1-800-361-7872 or email questions@reckeweg.com

PACKAGE LABEL

NDC# 53346-1309-5

Dr. Reckeweg R9 Jutussin

Homeopathic preparation for the temporary relief of:

- Cough due to common cold

Manufactured by:

Dr. Reckeweg Co. GmbH

D-64625 Bensheim

Germany

1.68 fl oz
(50 ml)